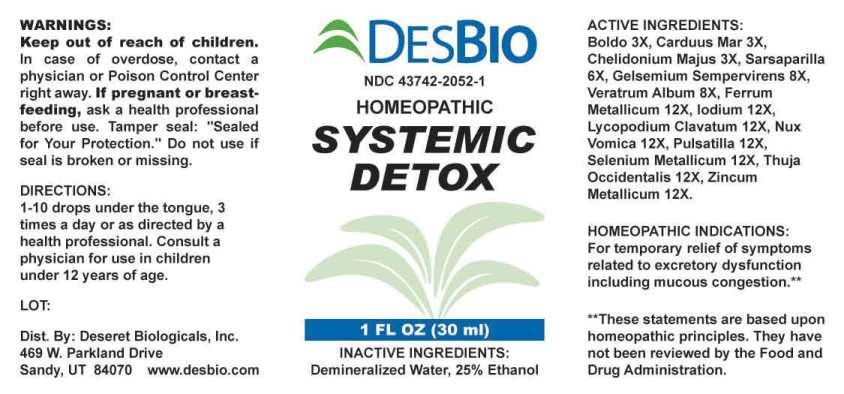 DRUG LABEL: Systemic Detox
NDC: 43742-2052 | Form: LIQUID
Manufacturer: Deseret Biologicals, Inc.
Category: homeopathic | Type: HUMAN OTC DRUG LABEL
Date: 20221011

ACTIVE INGREDIENTS: PEUMUS BOLDUS LEAF 3 [hp_X]/1 mL; MILK THISTLE 3 [hp_X]/1 mL; CHELIDONIUM MAJUS WHOLE 3 [hp_X]/1 mL; SMILAX ORNATA ROOT 6 [hp_X]/1 mL; GELSEMIUM SEMPERVIRENS ROOT 8 [hp_X]/1 mL; VERATRUM ALBUM ROOT 8 [hp_X]/1 mL; IRON 12 [hp_X]/1 mL; IODINE 12 [hp_X]/1 mL; LYCOPODIUM CLAVATUM SPORE 12 [hp_X]/1 mL; STRYCHNOS NUX-VOMICA SEED 12 [hp_X]/1 mL; PULSATILLA PRATENSIS WHOLE 12 [hp_X]/1 mL; SELENIUM 12 [hp_X]/1 mL; THUJA OCCIDENTALIS LEAFY TWIG 12 [hp_X]/1 mL; ZINC 12 [hp_X]/1 mL
INACTIVE INGREDIENTS: WATER; ALCOHOL

DRUG FACTS:

ACTIVE INGREDIENTS:

Boldo 3X, Carduus Marianus 3X, Chelidonium Majus 3X, Sarsaparilla (Smilax Regelii) 6X, Gelsemium Sempervirens 8X, Veratrum Album 8X, Ferrum Metallicum 12X, Iodium 12X, Lycopodium Clavatum 12X, Nux Vomica 12X, Pulsatilla (Pratensis) 12X, Selenium Metallicum 12X, Thuja Occidentalis 12X, Zincum Metallicum 12X.

HOMEOPATHIC INDICATIONS:

For temporary relief of symptoms related to excretory dysfunction including mucous congestion.**

**These statements are based upon homeopathic principles. They have not been reviewed by the Food and Drug Administration.

WARNINGS:

Keep out of reach of children. In case of overdose, contact a physician or Poison Control Center right away.

If pregnant or breast-feeding, ask a health professional before use.

Tamper seal: "Sealed for Your Protection." Do not use if seal is broken or missing.

Keep out of reach of children. In case of overdose, contact a physician or Poison Control Center right away.

DIRECTIONS:

1-10 drops under the tongue, 3 times a day or as directed by a health professional. Consult a physician for use in children under 12 years of age.

HOMEOPATHIC INDICATIONS:

For temporary relief of symptoms related to excretory dysfunction including mucous congestion.**

**These statements are based upon homeopathic principles. They have not been reviewed by the Food and Drug Administration.

INACTIVE INGREDIENTS:

Demineralized Water, 25% Ethanol

QUESTIONS:

Dist. By: Deseret Biologicals, Inc.

469 W. Parkland Drive

Sandy, UT 84070 www.desbio.com

PACKAGE LABEL DISPLAY:

DESBIO

NDC 43742-2052-1

HOMEOPATHIC

SYSTEMIC

DETOX

1 FL OZ (30 ml)